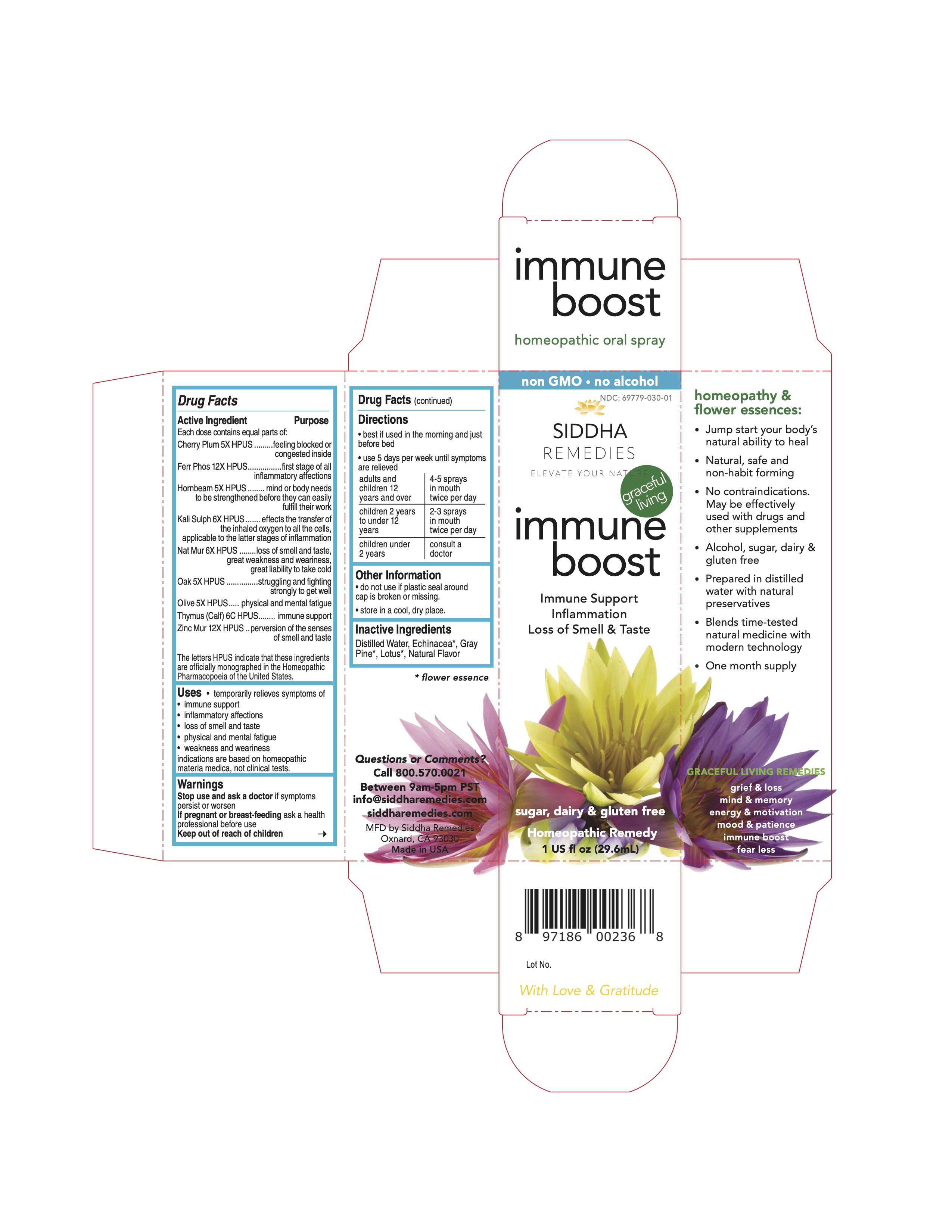 DRUG LABEL: Immune Boost
NDC: 69779-030 | Form: SPRAY
Manufacturer: Siddha Flower Essences LLC
Category: homeopathic | Type: HUMAN OTC DRUG LABEL
Date: 20251231

ACTIVE INGREDIENTS: QUERCUS ROBUR FLOWER 5 [hp_X]/29.6 mL; OLEA EUROPAEA FLOWER 5 [hp_X]/29.6 mL; SODIUM CHLORIDE 6 [hp_X]/29.6 mL; PRUNUS CERASIFERA FLOWER 5 [hp_X]/29.6 mL; ZINC CHLORIDE 12 [hp_X]/29.6 mL; FERROSOFERRIC PHOSPHATE 12 [hp_X]/29.6 mL; CARPINUS BETULUS FLOWER 5 [hp_X]/29.6 mL; BOS TAURUS THYMUS 6 [hp_C]/29.6 mL; POTASSIUM SULFATE 6 [hp_X]/29.6 mL
INACTIVE INGREDIENTS: PINUS SABINIANA WHOLE; WATER; ECHINACEA PURPUREA FLOWERING TOP

Purpose

Each dose contains equal parts of:

Cherry Plum 5X HPUS.........feeling blocked or congested inside

Ferr Phos 12X HPUS................first stage of all inflammatory affections

Hornbeam 5X HPUS........mind or body needsto be strengthened before they can easily fulfull their work

Kali Sulph 6X HPUS.......effects the transfer ofthe inhaled oxygen to all the cells, apllicable to the latter stages of innflamation

Nat Mur 6X HPUS........loss of smell and taste,great weakness and weariness,great liability to take coldOak 5X HPUS...............struggling and fightingstrongly to get well

Olive 5X HPUS.....physical and mental fatigue

Thymus (Calf) 6C HPUS...............immune support

Zinc Mur 12X HPUS..perversion of the senses of smell and taste

The letters HPUS indicate that these ingredients are officially monographed in the Homeopathic Pharmacopoeia of the United States.

Purpose

Each dose contains equal parts of:

Cherry Plum 5X HPUS.........feeling blocked or congested inside

Ferr Phos 12X HPUS................first stage of all inflammatory affections

Hornbeam 5X HPUS........mind or body needsto be strengthened before they can easily fulfull their work

Kali Sulph 6X HPUS.......effects the transfer ofthe inhaled oxygen to all the cells, apllicable to the latter stages of innflamation

Nat Mur 6X HPUS........loss of smell and taste,great weakness and weariness,great liability to take coldOak 5X HPUS...............struggling and fightingstrongly to get well

Olive 5X HPUS.....physical and mental fatigue

Thymus (Calf) 6C HPUS...............immune support

Zinc Mur 12X HPUS..perversion of the senses of smell and taste

The letters HPUS indicate that these ingredients are officially monographed in the Homeopathic Pharmacopoeia of the United States.

Uses

• temporarily relieves symptoms of

• immune support

• inflammatory affections

• loss of smell and taste

• physical and mental fatigue

• weakness and weariness

indications are based on homeopathic materia medica, not clinical tests.

Warnings

Stop use and ask a doctor if symptoms persist or worsen

If pregnant or breast-feeding ask a health professional before use

Keep out of reach of children

Keep out of reach of children

PREGNANCY OR BREAST FEEDING

If pregnant or breast-feeding ask a health professional before use

DOSAGE AND ADMINISTRATION

• best if used in the morning and just before bed

• use 5 days per week until symptoms are relieved

adults and children 12 years and over 4-5 sprays in mouth twice per day

children 2 years to under 12 years 2-3 sprays in mouth twice per day

children under 2 years consult a doctor

• do not use if plastic seal around cap is broken or missing.

• store in a cool, dry place.

Inactive Ingredients

Distilled Water, Echinacea*, Gray Pine*, Lotus*, Natural Flavor

Questions or Comments?

Call 800.570.0021

Between 9am-5pm PST

info@siddharemedies.com

siddharemedies.com

MFD by Siddha Remedies

Oxnard, CA 93030

Made in USA

Side Panel

homeopathy & flower essences:

• Jump start your body’snatural ability to heal

• Natural, safe and non-habit forming

• No contraindications. May be effectively used with drugs and other supplements

• Alcohol, sugar, dairy & gluten free

• Prepared in distilled water with natural preservatives

• Blends time-tested natural medicine with modern technology

• One month supply

Full Warning Panel

Warnings

Stop use and ask a doctor if symptoms

persist or worsen

If pregnant or breast-feeding ask a

health professional before use

Keep out of reach of children

PACKAGE LABEL

non GMO • no alcohol sugar, dairy & gluten free

Homeopathic Remedy

1 US fl oz (29.6mL)

NDC: 69779-030-01

mmuneboost

Immune Support

Inflammation

Loss of Smell & Taste